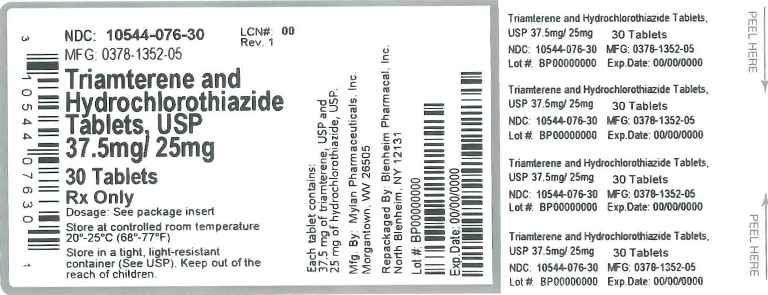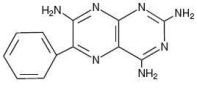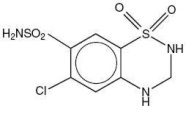 DRUG LABEL: Triamterene and Hydrochlorothiazide
NDC: 10544-076 | Form: TABLET
Manufacturer: Blenheim Pharmacal, Inc.
Category: prescription | Type: HUMAN PRESCRIPTION DRUG LABEL
Date: 20150313

ACTIVE INGREDIENTS: TRIAMTERENE 37.5 mg/1 1; HYDROCHLOROTHIAZIDE 25 mg/1 1
INACTIVE INGREDIENTS: SILICON DIOXIDE; CROSCARMELLOSE SODIUM; D&C YELLOW NO. 10; MAGNESIUM STEARATE; CELLULOSE, MICROCRYSTALLINE; POWDERED CELLULOSE; SODIUM LAURYL SULFATE; FD&C BLUE NO. 1

CLINICAL PHARMACOLOGY

Triamterene and hydrochlorothiazide is a diuretic, antihypertensive drug product, principally due to its hydrochlorothiazide component; the triamterene component reduces the excessive potassium loss which may occur with hydrochlorothiazide use.

Hydrochlorothiazide

Hydrochlorothiazide is a diuretic and antihypertensive agent. It blocks the renal tubular absorption of sodium and chloride ions. This natriuresis and diuresis is accompanied by a secondary loss of potassium and bicarbonate. Onset of hydrochlorothiazide's diuretic effect occurs within 2 hours and the peak action takes place in 4 hours. Diuretic activity persists for approximately 6 to 12 hours.

The exact mechanism of hydrochlorothiazide's antihypertensive action is not known although it may relate to the excretion and redistribution of body sodium. Hydrochlorothiazide does not affect normal blood pressure.

Following oral administration, peak hydrochlorothiazide plasma levels are attained in approximately 2 hours. It is excreted rapidly and unchanged in the urine.

Well controlled studies have demonstrated that doses of hydrochlorothiazide as low as 25 mg given once daily are effective in treating hypertension, but the dose-response has not been clearly established.

Triamterene

Triamterene is a potassium-conserving (antikaliuretic) diuretic with relatively weak natriuretic properties. It exerts its diuretic effect on the distal renal tubule to inhibit the reabsorption of sodium in exchange for potassium and hydrogen. With this action, triamterene increases sodium excretion and reduces the excessive loss of potassium and hydrogen associated with hydrochlorothiazide. Triamterene is not a competitive antagonist of the mineralocorticoids and its potassium-conserving effect is observed in patients with Addison's disease, i.e., without aldosterone. Triamterene's onset and duration of activity is similar to hydrochlorothiazide. No predictable antihypertensive effect has been demonstrated with triamterene.

Triamterene is rapidly absorbed following oral administration. Peak plasma levels are achieved within one hour after dosing. Triamterene is primarily metabolized to the sulfate conjugate of hydroxytriamterene. Both the plasma and urine levels of this metabolite greatly exceed triamterene levels.

The amount of triamterene added to 50 mg of hydrochlorothiazide in triamterene and hydrochlorothiazide 75 mg/50 mg tablets was determined from steady-state dose-response evaluations in which various doses of liquid preparations of triamterene were administered to hypertensive persons who developed hypokalemia with hydrochlorothiazide (50 mg given once daily). Single daily doses of 75 mg triamterene resulted in greater increases in serum potassium than lower doses (25 mg and 50 mg), while doses greater than 75 mg of triamterene resulted in no additional elevations in serum potassium levels. The amount of triamterene added to the 25 mg of hydrochlorothiazide in triamterene and hydrochlorothiazide 37.5 mg/25 mg tablets was also determined from steady-state dose-response evaluations in which various doses of liquid preparations of triamterene were administered to hypertensive persons who developed hypokalemia with hydrochlorothiazide (25 mg given once daily). Single daily doses of 37.5 mg triamterene resulted in greater increases in serum potassium than a lower dose (25 mg), while doses greater than 37.5 mg of triamterene, i.e., 75 mg and 100 mg, resulted in no additional elevations in serum potassium levels. The dose-response relationship of triamterene was also evaluated in patients rendered hypokalemic by hydrochlorothiazide given 25 mg twice daily. Triamterene given twice daily increased serum potassium levels in a dose related fashion. However, the combination of triamterene and hydrochlorothiazide given twice daily also appeared to produce an increased frequency of elevation in serum BUN and creatinine levels. The largest increases in serum potassium, BUN and creatinine in this study were observed with 50 mg of triamterene given twice daily, the largest dose tested. Ordinarily, triamterene does not entirely compensate for the kaliuretic effect of hydrochlorothiazide and some patients may remain hypokalemic while receiving triamterene and hydrochlorothiazide. In some individuals, however, it may induce hyperkalemia (see WARNINGS).

The triamterene and hydrochlorothiazide components of this product are well absorbed and are bioequivalent to liquid preparations of the individual components administered orally. Food does not influence the absorption of triamterene or hydrochlorothiazide from Triamterene and Hydrochlorothiazide Tablets. The hydrochlorothiazide component of triamterene and hydrochlorothiazide tablets is bioequivalent to single entity hydrochlorothiazide tablet formulations.

INDICATIONS AND USAGE

This fixed combination drug is not indicated for the initial therapy of edema or hypertension except in individuals in whom the development of hypokalemia cannot be risked.

- Triamterene and hydrochlorothiazide tablets are indicated for the treatment of hypertension or edema in patients who develop hypokalemia on hydrochlorothiazide alone.
- Triamterene and hydrochlorothiazide tablets are also indicated for those patients who require a thiazide diuretic and in whom the development of hypokalemia cannot be risked (e.g., patients on concomitant digitalis preparations, or with a history of cardiac arrhythmias, etc.).

Triamterene and hydrochlorothiazide tablets may be used alone or in combination with other antihypertensive drugs, such as beta-blockers. Since triamterene and hydrochlorothiazide tablets may enhance the actions of these drugs, dosage adjustments may be necessary.

Usage in Pregnancy

The routine use of diuretics in an otherwise healthy woman is inappropriate and exposes mother and fetus to unnecessary hazard. Diuretics do not prevent development of toxemia of pregnancy, and there is no satisfactory evidence that they are useful in the treatment of developed toxemia.

Edema during pregnancy may arise from pathological causes or from the physiologic and mechanical consequences of pregnancy. Thiazides are indicated in pregnancy when edema is due to pathologic causes, just as they are in the absence of pregnancy. Dependent edema in pregnancy, resulting from restriction of venous return by the expanded uterus, is properly treated through elevation of the lower extremities and use of support hose; use of diuretics to lower intravascular volume in this case is illogical and unnecessary. There is hypervolemia during normal pregnancy which is harmful to neither the fetus nor the mother (in the absence of cardiovascular disease), but which is associated with edema, including generalized edema, in the majority of pregnant women. If this edema produces discomfort, increased recumbency will often provide relief. In rare instances, this edema may cause extreme discomfort which is not relieved by rest. In these cases, a short course of diuretics may provide relief and may be appropriate.

CONTRAINDICATIONS

Hyperkalemia

Triamterene and hydrochlorothiazide should not be used in the presence of elevated serum potassium levels (greater than or equal to 5.5 mEq/liter). If hyperkalemia develops, this drug should be discontinued and a thiazide alone should be substituted.

Antikaliuretic Therapy or Potassium Supplementation

Triamterene and hydrochlorothiazide should not be given to patients receiving other potassium-conserving agents such as spironolactone, amiloride hydrochloride or other formulations containing triamterene. Concomitant potassium supplementation in the form of medication, potassium-containing salt substitute or potassium-enriched diets should also not be used.

Impaired Renal Function

Triamterene and hydrochlorothiazide is contraindicated in patients with anuria, acute and chronic renal insufficiency or significant renal impairment.

Hypersensitivity

Triamterene and hydrochlorothiazide should not be used in patients who are hypersensitive to triamterene or hydrochlorothiazide or other sulfonamide-derived drugs.

WARNINGS

WARNINGS

Hyperkalemia

Abnormal elevation of serum potassium levels (greater than or equal to 5.5 mEq/liter) can occur with all potassium-conserving diuretic combinations, including triamterene and hydrochlorothiazide. Hyperkalemia is more likely to occur in patients with renal impairment, diabetes (even without evidence of renal impairment), or elderly or severely ill patients. Since uncorrected hyperkalemia may be fatal, serum potassium levels must be monitored at frequent intervals especially in patients first receiving triamterene and hydrochlorothiazide, when dosages are changed or with any illness that may influence renal function.

If hyperkalemia is suspected, (warning signs include paresthesias, muscular weakness, fatigue, flaccid paralysis of the extremities, bradycardia and shock) an electrocardiogram (ECG) should be obtained. However, it is important to monitor serum potassium levels because mild hyperkalemia may not be associated with ECG changes.

If hyperkalemia is present, triamterene and hydrochlorothiazide should be discontinued immediately and a thiazide alone should be substituted. If the serum potassium exceeds 6.5 mEq/liter, more vigorous therapy is required. The clinical situation dictates the procedures to be employed. These include the intravenous administration of calcium chloride solution, sodium bicarbonate solution and/or the oral or parenteral administration of glucose with a rapid-acting insulin preparation. Cationic exchange resins such as sodium polystyrene sulfonate may be orally or rectally administered. Persistent hyperkalemia may require dialysis.

The development of hyperkalemia associated with potassium-sparing diuretics is accentuated in the presence of renal impairment (see CONTRAINDICATIONS). Patients with mild renal functional impairment should not receive this drug without frequent and continuing monitoring of serum electrolytes. Cumulative drug effects may be observed in patients with impaired renal function. The renal clearances of hydrochlorothiazide and the pharmacologically active metabolite of triamterene, the sulfate ester of hydroxytriamterene, have been shown to be reduced and the plasma levels increased following triamterene and hydrochlorothiazide administration to elderly patients and patients with impaired renal function.

Hyperkalemia has been reported in diabetic patients with the use of potassium-conserving agents even in the absence of apparent renal impairment. Accordingly, triamterene and hydrochlorothiazide should be avoided in diabetic patients. If it is employed, serum electrolytes must be frequently monitored.

Because of the potassium-sparing properties of angiotensin-converting enzyme (ACE) inhibitors, triamterene and hydrochlorothiazide should be used cautiously, if at all, with these agents (see PRECAUTIONS: Drug Interactions).

Metabolic or Respiratory Acidosis

Potassium-conserving therapy should also be avoided in severely ill patients in whom respiratory or metabolic acidosis may occur. Acidosis may be associated with rapid elevations in serum potassium levels. If triamterene and hydrochlorothiazide is employed, frequent evaluations of acid/base balance and serum electrolytes are necessary.

Acute Myopia and Secondary Angle-Closure Glaucoma

Hydrochlorothiazide, a sulfonamide, can cause an idiosyncratic reaction, resulting in acute transient myopia and acute angle-closure glaucoma. Symptoms include acute onset of decreased visual acuity or ocular pain and typically occur within hours to weeks of drug initiation. Untreated acute angle-closure glaucoma can lead to permanent vision loss. The primary treatment is to discontinue hydrochlorothiazide as rapidly as possible. Prompt medical or surgical treatments may need to be considered if the intraocular pressure remains uncontrolled. Risk factors for developing acute angle-closure glaucoma may include a history of sulfonamide or penicillin allergy.

PRECAUTIONS

General

Electrolyte Imbalance and BUN Increases

Patients receiving triamterene and hydrochlorothiazide should be carefully monitored for fluid or electrolyte imbalances, i.e., hyponatremia, hypochloremic alkalosis, hypokalemia and hypomagnesemia. Determination of serum electrolytes to detect possible electrolyte imbalance should be performed at appropriate intervals. Serum and urine electrolyte determinations are especially important and should be frequently performed when the patient is vomiting or receiving parenteral fluids. Warning signs or symptoms of fluid and electrolyte imbalance include: dryness of mouth, thirst, weakness, lethargy, drowsiness, restlessness, muscle pains or cramps, muscular fatigue, hypotension, oliguria, tachycardia and gastrointestinal disturbances such as nausea and vomiting.

Any chloride deficit during thiazide therapy is generally mild and usually does not require any specific treatment except under extraordinary circumstances (as in liver disease or renal disease). Dilutional hyponatremia may occur in edematous patients in hot weather; appropriate therapy is water restriction, rather than administration of salt, except in rare instances when the hyponatremia is life threatening. In actual salt depletion, appropriate replacement is the therapy of choice.

Hypokalemia may develop with thiazide therapy, especially with brisk diuresis, when severe cirrhosis is present, or during concomitant use of corticosteroids, ACTH, amphotericin B or after prolonged thiazide therapy. However, hypokalemia of this type is usually prevented by the triamterene component of triamterene and hydrochlorothiazide.

Interference with adequate oral electrolyte intake will also contribute to hypokalemia. Hypokalemia can sensitize or exaggerate the response of the heart to the toxic effects of digitalis (e.g., increased ventricular irritability).

Triamterene and hydrochlorothiazide may produce an elevated blood urea nitrogen level (BUN), creatinine level or both. This is probably not the result of renal toxicity but is secondary to a reversible reduction of the glomerular filtration rate or a depletion of the intravascular fluid volume. Elevations in BUN and creatinine levels may be more frequent in patients receiving divided dose diuretic therapy. Periodic BUN and creatinine determinations should be made especially in elderly patients, patients with suspected or confirmed hepatic disease or renal insufficiencies. If azotemia increases, triamterene and hydrochlorothiazide should be discontinued.

Hepatic Coma

Triamterene and hydrochlorothiazide should be used with caution in patients with impaired hepatic function or progressive liver disease, since minor alterations of fluid and electrolyte balance may precipitate hepatic coma.

Renal Stones

Triamterene has been reported in renal stones in association with other calculus components. Triamterene and hydrochlorothiazide should be used with caution in patients with histories of renal lithiasis.

Folic Acid Deficiency

Triamterene is a weak folic acid antagonist and may contribute to the appearance of megaloblastosis in instances where folic acid stores are decreased. In such patients, periodic blood elevations are recommended.

Hyperuricemia

Hyperuricemia may occur or acute gout may be precipitated in certain patients receiving thiazide therapy.

Metabolic and Endocrine Effects

The thiazides may decrease serum PBI levels without signs of thyroid disturbance.

Calcium excretion is decreased by thiazides. Pathological changes in the parathyroid gland with hypercalcemia and hypophosphatemia have been observed in a few patients on prolonged thiazide therapy. The common complications of hyperparathyroidism such as renal lithiasis, bone resorption, and peptic ulceration have not been seen. Thiazides should be discontinued before carrying out tests for parathyroid function.

Insulin requirements in diabetic patients may be increased, decreased or unchanged. Diabetes mellitus which has been latent may become manifest during thiazide administration.

Hypersensitivity

Sensitivity reactions to thiazides may occur in patients with or without a history of allergy or bronchial asthma.

Possible exacerbation or activation of systemic lupus erythematosus by thiazides has been reported.

Drug Interactions

Thiazides may add to or potentiate the action of other antihypertensive drugs.

The thiazides may decrease arterial responsiveness to norepinephrine. This diminution is not sufficient to preclude effectiveness of the pressor agent for therapeutic use. Thiazides have also been shown to increase the responsiveness to tubocurarine.

Lithium generally should not be given with diuretics because they reduce its renal clearance and add a high risk of lithium toxicity. Refer to the package insert on lithium before use of such concomitant therapy.

Acute renal failure has been reported in a few patients receiving indomethacin and formulations containing triamterene and hydrochlorothiazide. Caution is therefore advised when administering non-steroidal anti-inflammatory agents with triamterene and hydrochlorothiazide.

Potassium-sparing agents should be used very cautiously, if at all, in conjunction with angiotensin-converting enzyme (ACE) inhibitors due to a greatly increased risk of hyperkalemia. Serum potassium should be monitored frequently.

Drug/Laboratory Test Interactions

Triamterene and quinidine have similar fluorescence spectra; thus triamterene and hydrochlorothiazide may interfere with the measurement of quinidine.

Carcinogenesis, Mutagenesis, Impairment of Fertility

Carcinogenesis

Long term studies with triamterene and hydrochlorothiazide have not been conducted.

Triamterene

In studies conducted under the auspices of the National Toxicology Program, groups of rats were fed diets containing 0, 150, 300 or 600 ppm triamterene, and groups of mice were fed diets containing 0, 100, 200 or 400 ppm triamterene. Male and female rats exposed to the highest tested concentration received triamterene at about 25 and 30 mg/kg/day, respectively. Male and female mice exposed to the highest tested concentration received triamterene at about 45 and 60 mg/kg/day, respectively.

There was an increased incidence of hepatocellular neoplasia (primarily adenomas) in male and female mice at the highest dosage level. These doses represent 7.5 times and 10 times the MRHD of 300 mg/kg (or 6 mg/kg/day based on a 50 kg patient) for male and female mice, respectively when based on body-weight and 0.7 times and 0.9 times the MRHD when based on body-surface area. Although hepatocellular neoplasia (exclusively adenomas) in the rat study was limited to triamterene-exposed males, incidence was not dose dependent and there was no statistically significant difference from control incidence at any dose level.

Hydrochlorothiazide

Two-year feeding studies in mice and rats, conducted under the auspices of the National Toxicology Program (NTP), treated mice and rats with doses of hydrochlorothiazide up to 600 and 100 mg/kg/day, respectively. On a body-weight basis, these doses are 600 times (in mice) and 100 times (in rats) the Maximum Recommended Human Dose (MRHD) for hydrochlorothiazide (50 mg/day or 1 mg/kg/day based on a 50 kg patient). On the basis of body-surface area, these doses are 56 times (in mice) and 21 times (in rats) the MRHD. These studies uncovered no evidence of carcinogenic potential of hydrochlorothiazide in rats or female mice, but there was equivocal evidence of hepatocarcinogenicity in male mice.

Mutagenesis

Studies of the mutagenic potential of triamterene and hydrochlorothiazide have not been performed.

Triamterene

Triamterene was not mutagenic in bacteria (S. typhimurium strains TA 98, TA 100, TA 1535 or TA 1537) with or without metabolic activation. It did not induce chromosomal aberrations in Chinese hamster ovary (CHO) cells in vitro with or without metabolic activation, but it did induce sister chromatid exchanges in CHO cells in vitro with and without metabolic activation.

Hydrochlorothiazide

Hydrochlorothiazide was not genotoxic in in vitro assays using strains TA 98, TA 100, TA 1535, TA 1537 and TA 1538 of Salmonella typhimurium (the Ames test), in the Chinese hamster ovary (CHO) test for chromosomal aberrations, or in in vivo assays using mouse germinal cell chromosomes, Chinese hamster bone marrow chromosomes, and the Drosophila sex-linked recessive lethal trait gene. Positive test results were obtained in the in vitro CHO sister chromatid exchange (clastogenicity) test, and in the mouse lymphoma cell (mutagenicity) assays, using concentrations of hydrochlorothiazide of 43 to 1300 mcg/mL. Positive test results were also obtained in the Aspergillus nidulans nondisjunction assay using an unspecified concentration of hydrochlorothiazide.

Impairment of Fertility

Studies of the effects of triamterene and hydrochlorothiazide or of triamterene alone on animal reproductive function have not been conducted.

Hydrochlorothiazide

Hydrochlorothiazide had no adverse effects on the fertility of mice and rats of either sex in studies wherein these species were exposed, via their diet, to doses of up to 100 and 4 mg/kg/day, respectively, prior to mating and throughout gestation. Corresponding multiples of the MRHD are 100 (mice) and 4 (rats) on the basis of body-weight and 9.4 (mice) and 0.8 (rats) on the basis of body-surface area.

Pregnancy

Teratogenic Effects. Category C

Triamterene and Hydrochlorothiazide

Animal reproduction studies to determine the potential for fetal harm by triamterene and hydrochlorothiazide have not been conducted. Nevertheless, a One Generation Study in the rat approximated triamterene and hydrochlorothiazide's composition by using a 1:1 ratio of triamterene to hydrochlorothiazide (30:30 mg/kg/day). There was no evidence of teratogenicity at those doses that were, on a body-weight basis, 15 and 30 times, respectively, the MRHD, and, on the basis of body-surface area, 3.1 and 6.2 times, respectively, the MRHD.

The safe use of triamterene and hydrochlorothiazide in pregnancy has not been established since there are no adequate and well-controlled studies with triamterene and hydrochlorothiazide in pregnant women. Triamterene and hydrochlorothiazide should be used during pregnancy only if the potential benefit justifies the risk to the fetus.

Triamterene

Reproduction studies have been performed in rats at doses as high as 20 times the Maximum Recommended Human Dose (MRHD) on the basis of body-weight, and 6 times the MRHD on the basis of body-surface area without evidence of harm to the fetus due to triamterene.

Because animal reproduction studies are not always predictive of human response, this drug should be used during pregnancy only if clearly needed.

Hydrochlorothiazide

Hydrochlorothiazide was orally administered to pregnant mice and rats during respective periods of major organogenesis at doses up to 3000 and 1000 mg/kg/day, respectively. At these doses, which are multiples of the MRHD equal to 3000 for mice and 1000 for rats, based on body-weight, and equal to 282 for mice and 206 for rats, based on body-surface area, there was no evidence of harm to the fetus. There are, however, no adequate and well controlled studies in pregnant women. Because animal reproduction studies are not always predictive of human response, this drug should be used during pregnancy only if clearly needed.

Nonteratogenic Effects

Thiazides and triamterene have been shown to cross the placental barrier and appear in cord blood. The use of thiazides and triamterene in pregnant women requires that the anticipated benefits be weighed against possible hazards to the fetus. These hazards include fetal or neonatal jaundice, pancreatitis, thrombocytopenia, and possibly other adverse reactions that have occurred in the adult.

Nursing Mothers

Thiazides and triamterene in combination have not been studied in nursing mothers. Triamterene appears in animal milk and this may occur in humans. Thiazides are excreted in human breast milk. If use of the combination drug product is deemed essential, the patient should stop nursing.

Pediatric Use

Safety and effectiveness in pediatric patients have not been established.

ADVERSE REACTIONS

Side effects observed in association with the use of triamterene and hydrochlorothiazide tablets, other combination products containing triamterene/hydrochlorothiazide, and products containing triamterene or hydrochlorothiazide include the following:

Gastrointestinal: jaundice (intrahepatic cholestatic jaundice), pancreatitis, nausea, appetite disturbance, taste alteration, vomiting, diarrhea, constipation, anorexia, gastric irritation, cramping.

Central Nervous System: drowsiness and fatigue, insomnia, headache, dizziness, dry mouth, depression, anxiety, vertigo, restlessness, paresthesias.

Cardiovascular: tachycardia, shortness of breath and chest pain, orthostatic hypotension (may be aggravated by alcohol, barbiturates or narcotics).

Renal: acute renal failure, acute interstitial nephritis, renal stones composed of triamterene in association with other calculus materials, urine discoloration.

Hematologic: leukopenia, agranulocytosis, thrombocytopenia, aplastic anemia, hemolytic anemia and megaloblastosis.

Ophthalmic: xanthopsia, transient blurred vision.

Hypersensitivity: anaphylaxis, photosensitivity, rash, urticaria, purpura, necrotizing angiitis (vasculitis, cutaneous vasculitis), fever, respiratory distress including pneumonitis.

Other: muscle cramps and weakness, decreased sexual performance and sialadenitis.

Whenever adverse reactions are moderate to severe, therapy should be reduced or withdrawn.

Altered Laboratory Findings

Serum Electrolytes: hyperkalemia, hypokalemia, hyponatremia, hypomagnesemia, hypochloremia (see WARNINGS and PRECAUTIONS).

Creatinine, Blood Urea Nitrogen: Reversible elevations in BUN and serum creatinine have been observed in hypertensive patients treated with triamterene and hydrochlorothiazide.

Glucose: hyperglycemia, glycosuria and diabetes mellitus (see PRECAUTIONS).

Serum Uric Acid, PBI and Calcium: (see PRECAUTIONS).

Other: Elevated liver enzymes have been reported in patients receiving triamterene and hydrochlorothiazide.

OVERDOSAGE

No specific data are available regarding triamterene and hydrochlorothiazide overdosage in humans and no specific antidote is available.

Fluid and electrolyte imbalances are the most important concern. Excessive doses of the triamterene component may elicit hyperkalemia, dehydration, nausea, vomiting and weakness and possibly hypotension. Overdosing with hydrochlorothiazide has been associated with hypokalemia, hypochloremia, hyponatremia, dehydration, lethargy (may progress to coma) and gastrointestinal irritation. Treatment is symptomatic and supportive. Therapy with triamterene and hydrochlorothiazide should be discontinued. Induce emesis or institute gastric lavage. Monitor serum electrolyte levels and fluid balance. Institute supportive measures as required to maintain hydration, electrolyte balance, respiratory, cardiovascular and renal function.

DOSAGE AND ADMINISTRATION

The usual dose of Triamterene and Hydrochlorothiazide Tablets 37.5 mg/25 mg is one or two tablets daily, given as a single dose, with appropriate monitoring of serum potassium (see WARNINGS). The usual dose of Triamterene and Hydrochlorothiazide Tablets 75 mg/50 mg is one tablet daily, with appropriate monitoring of serum potassium (see WARNINGS). There is no experience with the use of more than one 75 mg/50 mg (75 mg triamterene and 50 mg hydrochlorothiazide) tablet daily or more than two 37.5 mg/25 mg (37.5 mg triamterene and 25 mg hydrochlorothiazide) tablets daily. Clinical experience with the administration of two 37.5 mg/25 mg tablets daily in divided doses (rather than as a single dose) suggests an increased risk of electrolyte imbalance and renal dysfunction.

Patients receiving 50 mg of hydrochlorothiazide who become hypokalemic may be transferred to this 75 mg/50 mg product directly. Patients receiving 25 mg hydrochlorothiazide who become hypokalemic may be transferred to this 37.5 mg/25 mg product directly.

In patients requiring hydrochlorothiazide therapy and in whom hypokalemia cannot be risked, therapy may be initiated with 37.5 mg/25 mg of triamterene and hydrochlorothiazide. If an optimal blood pressure response is not obtained with 37.5 mg/25 mg of triamterene and hydrochlorothiazide, the dose should be increased to two 37.5 mg/25 mg tablets daily as a single dose, or one 75 mg/50 mg tablet daily. If blood pressure still is not controlled, another antihypertensive agent may be added (see PRECAUTIONS: Drug Interactions).

Clinical studies have shown that patients taking less bioavailable formulations of triamterene and hydrochlorothiazide in daily doses of 25 mg to 50 mg hydrochlorothiazide and 50 mg to 100 mg triamterene may be safely changed to one triamterene and hydrochlorothiazide 37.5 mg/25 mg tablet daily. All patients changed from less bioavailable formulations to this product should be monitored clinically and for serum potassium after the transfer.

HOW SUPPLIED

Triamterene and Hydrochlorothiazide Tablets, USP are available as follows:

The 37.5 mg/25 mg tablets are green round tablets debossed with MYLAN on one side of the tablet and TH above the score and 1 below the score on the other side. They are available as follows:

NDC 0378-1352-01
bottles of 100 tablets

NDC 0378-1352-05
bottles of 500 tablets

The 75 mg/50 mg tablets are yellow round tablets debossed with MYLAN on one side of the tablet and TH above the score and 2 below the score on the other side. They are available as follows:

NDC 0378-1355-01
bottles of 100 tablets

NDC 0378-1355-05
bottles of 500 tablets

Store at 20° to 25°C (68° to 77°F). [See USP Controlled Room Temperature.]

Protect from light.

Dispense in a tight, light-resistant container as defined in the USP using a child-resistant closure.

Mylan Pharmaceuticals Inc.
Morgantown, WV 26505 U.S.A.

REVISED JANUARY 2011
TRHCT:R4

DESCRIPTION

Triamterene and hydrochlorothiazide combines triamterene, a potassium-conserving diuretic, with the natriuretic agent, hydrochlorothiazide.

Each Triamterene and Hydrochlorothiazide Tablet, USP 37.5 mg/25 mg contains:

Triamterene, USP . . . . . . . . 37.5 mg
Hydrochlorothiazide, USP . . . 25 mg

Each Triamterene and Hydrochlorothiazide Tablet, USP 75 mg/50 mg contains:

Triamterene, USP . . . . . . . . . . 75 mg
Hydrochlorothiazide, USP . . . . 50 mg

Triamterene and hydrochlorothiazide tablets for oral administration contain the following inactive ingredients: colloidal silicon dioxide, croscarmellose sodium, D&C Yellow No. 10 Aluminum Lake, magnesium stearate, microcrystalline cellulose, powdered cellulose and sodium lauryl sulfate. Additionally, the 37.5 mg/25 mg product contains FD&C Blue No. 1 Aluminum Lake.

Triamterene is 2,4,7-triamino-6-phenylpteridine. Triamterene is practically insoluble in water, benzene, chloroform, ether and dilute alkali hydroxides. It is soluble in formic acid and sparingly soluble in methoxyethanol. Triamterene is very slightly soluble in acetic acid, alcohol and dilute mineral acids. Its molecular weight is 253.27. Its structural formula is:

Hydrochlorothiazide is 6-chloro-3,4-dihydro-2 H-1,2,4, benzothiadiazine-7-sulfonamide 1,1-dioxide. Hydrochlorothiazide is slightly soluble in water and freely soluble in sodium hydroxide solution, n-butylamine and dimethylformamide. It is sparingly soluble in methanol and insoluble in ether, chloroform and dilute mineral acids. Its molecular weight is 297.73. Its structural formula is:

Principal Display Panel

Blenheim Pharmacal, Inc.

NDC 10544-076-30

Triamterene and Hydrochlorothiazide Tablets, USP 37.5mg/25mg

30 Tablets